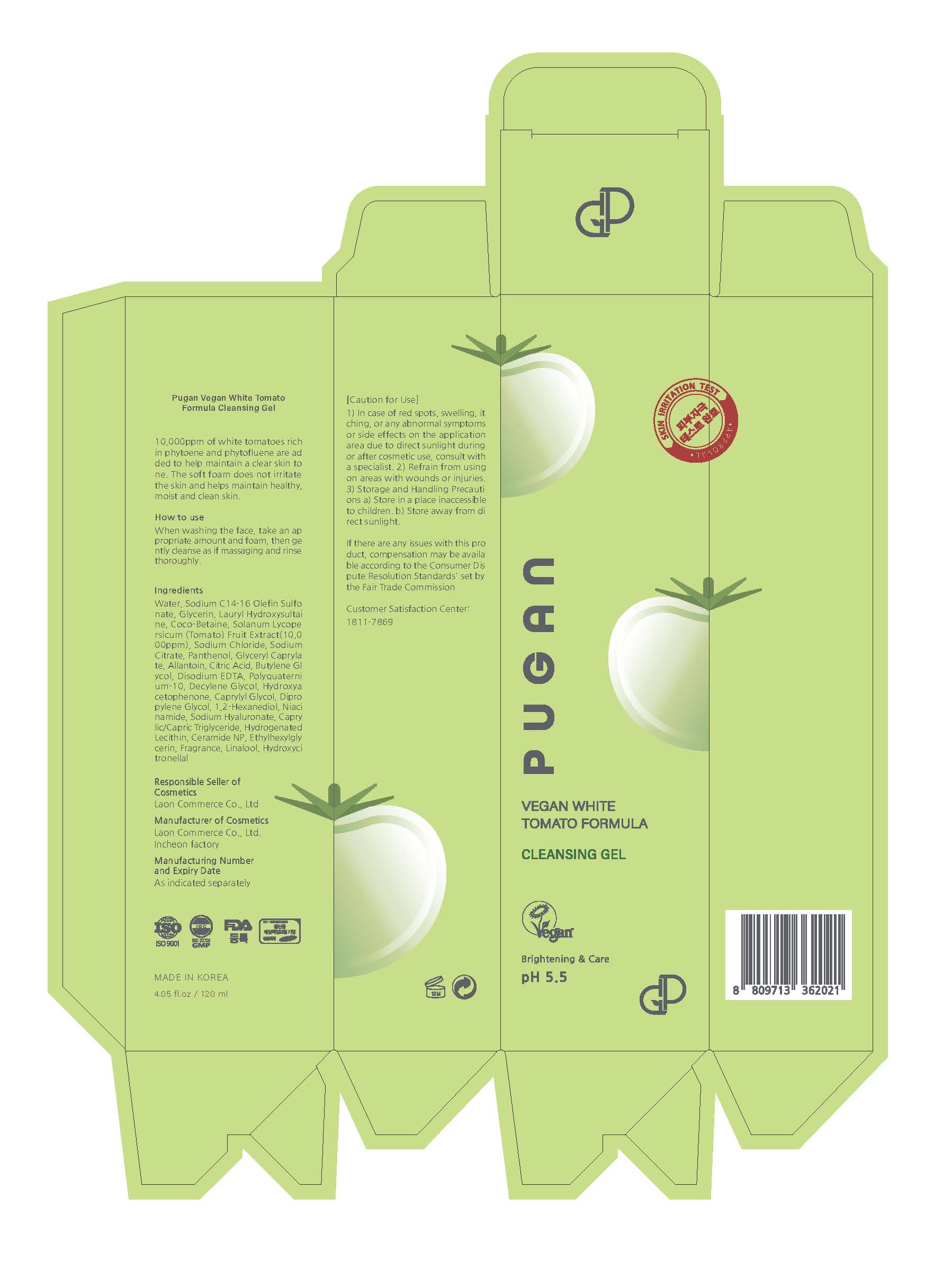 DRUG LABEL: Pugan vegan White Tomato formula Cleansing Gel
NDC: 82083-0029 | Form: GEL
Manufacturer: LAON COMMERCE co ltd
Category: otc | Type: HUMAN OTC DRUG LABEL
Date: 20240124

ACTIVE INGREDIENTS: NIACINAMIDE 0.01 g/100 mL
INACTIVE INGREDIENTS: WATER; SOLANUM LYCOPERSICUM

ACTIVE INGREDIENT

Niacinamide

INACTIVE INGREDIENT

Water
Sodium C14-16 Olefin Sulfonate

Glycerin

Lauryl Hydroxysultaine

Coco-Betaine

Cocamidopropyl Betaine

Solanum Lycopersicum (Tomato) Fruit Extract

Sodium Citrate

Panthenol

Sodium Chloride

Glyceryl Caprylate

Disodium EDTA

Citric Acid

Allantoin

Polyquaternium-10

Decylene Glycol

Dipropylene Glycol

Caprylyl Glycol

Hydroxyacetophenone

1,2-Hexanediol

Lactic Acid

Sodium Hyaluronate

Caprylic/Capric Triglyceride

Hydrogenated Lecithin

Ceramide NP

Ethylhexylglycerin

Fragrance

PURPOSE

skin protect

KEEP OUT OF REACH OF THE CHILDREN

INDICATIONS AND USAGE

When washing the face, take an appropriate amount and foam, then gently cleanse as if massaging and rinse thoroughly.

WARNINGS

abno rmal symptoms or side effects on the application
area
due to direct sunlight during or af ter cosmetic use,
consult with a specialist.
2) Refrain from using
on areas with wounds or injuries.
3
) Storage and Handling Precautio ns
a)
Store in a place inacces sible to children.
b) Store away from di
rect sunlight.

DOSAGE AND ADMINISTRATION

topical use only